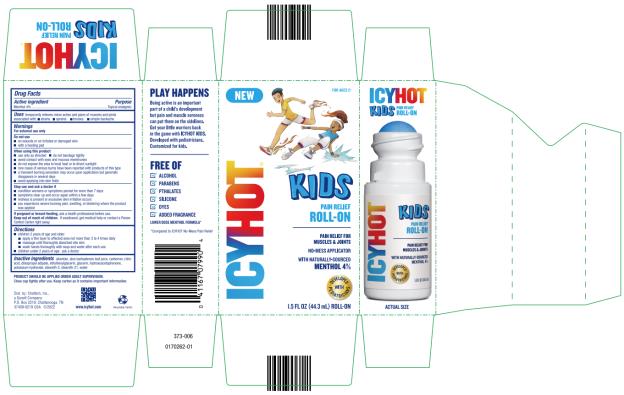 DRUG LABEL: Icy Hot Kids Pain Relief Roll-On
NDC: 41167-0799 | Form: LIQUID
Manufacturer: Chattem, Inc.
Category: otc | Type: HUMAN OTC DRUG LABEL
Date: 20231025

ACTIVE INGREDIENTS: MENTHOL 4 g/100 mL
INACTIVE INGREDIENTS: ALLANTOIN; ALOE VERA LEAF; CARBOMER HOMOPOLYMER, UNSPECIFIED TYPE; CITRIC ACID MONOHYDRATE; DIISOPROPYL ADIPATE; ETHYLHEXYLGLYCERIN; GLYCERIN; HYDROXYACETOPHENONE; POTASSIUM HYDROXIDE; STEARETH-2; STEARETH-21; WATER

Icy Hot Kids Pain Relief Roll-On

Icy Hot Kids Pain Relief Roll-On

Drug Facts

Purpose

Menthol 4%.........................................................................................................................Topical analgesic

Uses

temporarily relieves minor aches and pains of muscles and joints associated with: ■ strains

■ sprains ■ bruises ■ simple backache

Warnings

For external use only

Do not use

■ on wounds or on irritated or damaged skin

■ with a heating pad

When using this product

■ use only as directed

■ do not bandage tightly

■ avoid contact with eyes and mucous membranes

■ do not expose the area to local heat or to direct sunlight

■ rare cases of serious burns have been reported with products of this type

■ a transient burning sensation may occur upon application but generally disappears in several days

■ avoid applying into skin folds

Stop use and ask a doctor if

■ condition worsens or symptoms persist for more than 7 days

■ symptoms clear up and occur again within a few days

■ redness is present or excessive skin irritation occurs

■ you experience severe burning pain, swelling, or blistering where the product was applied

If pregnant or breast-feeding,

ask a health professional before use.

Keep out of reach of children.

If swallowed, get medical help or contact a Poison Control Center right away.

Directions

■ children 2 years of age and older:

■ apply a thin layer to affected area not more than 3 to 4 times daily

■ massage until thoroughly absorbed into skin

■ wash hands thoroughly with soap and water after each use

■ children under 2 years of age: ask a doctor

Inactive ingredients

allantoin, aloe barbadensis leaf juice, carbomer, citric acid, diisopropyl adipate, ethylhexylglycerin, glycerin, hydroxyacetophenone, potassium hydroxide, steareth-2, steareth-21, water

PRODUCT SHOULD BE APPLIED UNDER ADULT SUPERVISION. Close cap tightly after use.

Keep carton as it contains important information.

PRINCIPAL DISPLAY PANEL

Icy Hot
Kids Pain Relief
Roll-On
1.5 FL OZ (44.3 mL) ROLL-ON